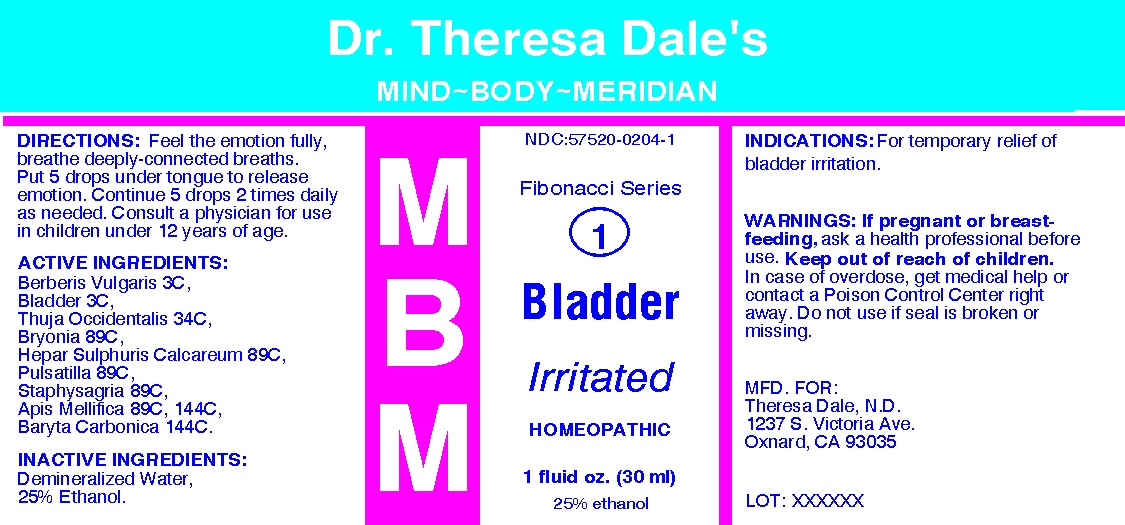 DRUG LABEL: MBM 1 Bladder Irritated
NDC: 57520-0204 | Form: LIQUID
Manufacturer: Apotheca Company
Category: homeopathic | Type: HUMAN OTC DRUG LABEL
Date: 20100707

ACTIVE INGREDIENTS: BERBERIS VULGARIS FRUIT 3 [hp_C]/1 mL; SUS SCROFA URINARY BLADDER 3 [hp_C]/1 mL; THUJA OCCIDENTALIS LEAFY TWIG 34 [hp_C]/1 mL; BRYONIA ALBA ROOT 89 [hp_C]/1 mL; CALCIUM SULFIDE 89 [hp_C]/1 mL; PULSATILLA VULGARIS 89 [hp_C]/1 mL; DELPHINIUM STAPHISAGRIA SEED 89 [hp_C]/1 mL; APIS MELLIFERA 144 [hp_C]/1 mL; BARIUM CARBONATE 144 [hp_C]/1 mL
INACTIVE INGREDIENTS: WATER; ALCOHOL

MBM 1 Bladder Irritated

ACTIVE INGREDIENT

ACTIVE INGREDIENTS: Berberis vulgaris 3C, Bladder 3C, Thuja occidentalis 34C, Bryonia 89C, Hepar sulphuris calcareum 89C, Pulsatilla 89C, Staphysagria 89C, Apis mellifica 89C, 144C, Baryta carbonica 144C.

PURPOSE

INDICATIONS: For temporary relief of bladder irritation.

WARNINGS

WARNINGS: If pregnant or breast-feeding, ask a health professional before use.

Keep out of reach of children. In case of overdose, get medical help or contact a Poison Control Center right away.

Do not use if seal is broken or missing.

DOSAGE AND ADMINISTRATION

DIRECTIONS: Feel the emotion fully, breathe deeply-connected breaths. Put 5 drops under tongue to release emotion. Continue 5 drops 2 times daily as needed. Consult a physician for use in children under 12 years of age.

INACTIVE INGREDIENTS: Demineralized water, 25% Ethanol

QUESTIONS

MFD. FOR:

Theresa Dale, N.D.

1237 S. Victoria Ave.

Oxnard, CA 93035

PACKAGE LABEL

Dr. Theresa Dale's

MIND-BODY-MERIDIAN

Fibonacci Series

1

BLADDER

IRRITATED

HOMEOPATHIC

1 fluid oz. (30 ml)